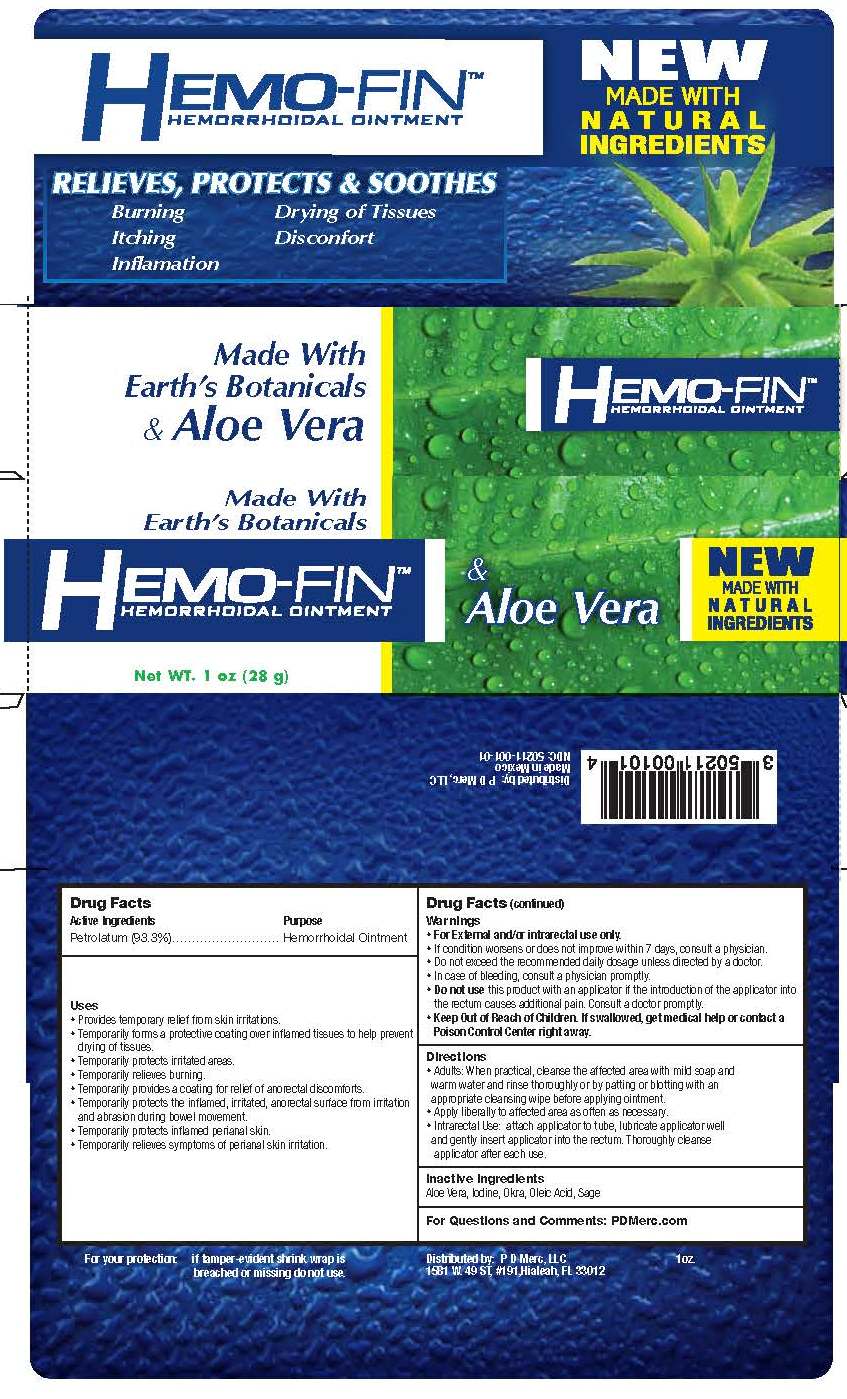 DRUG LABEL: Hemo Fin
NDC: 50211-001 | Form: OINTMENT
Manufacturer: PD MERC LLC
Category: otc | Type: HUMAN OTC DRUG LABEL
Date: 20120910

ACTIVE INGREDIENTS: Petrolatum 93.3 g/100 g
INACTIVE INGREDIENTS: Aloe Vera Leaf; Iodine; Okra; Oleic Acid; Sage

Hemo-Fin Hemorrhoidal Ointment

Active ingredient

Petrolatum (93.3%)

Purpose

Hemorrhoidal ointment

Uses

• Provides temporary relief from skin irritations
• Temporarily forms a protective coating over inflamed tissues to help prevent drying of tissues
• Temporarily protects irritated areas
• Temporarily relieves burning
• Temporarily provides a coating for relief of anorectal discomforts
• Temporarily protects the inflamed, irritated, anorectal surface from irritation and abrasion during bowel movement
• Temporarily protects inflamed perianal skin
• Temporarily relieves symptoms of perianal skin irritation

Warnings

For external and/or intrarectal use only

If condition worsens or does not improve within 7 days, consult a physician

Do not exceed the recommended daily dosage unless directed by a doctor

In case of bleeding, consult a physican promptly

Do not use

this product with an applicator if the introduction of the applicator into the rectum causes additional pain. Consult a doctor promptly.

Keep Out Of Reach of Children

If swallowed, get medical help or contact a Poison Control Center right away.

Directions

• Adults: When practical, cleanse the affected area with mild soap and warm water and rinse thoroughly or by patting or blotting with an appropriate cleansing wipe before applying ointment.
• Apply liberally to affected area as often as necessary.
• Intrarectal Use: attach applicator to tube, lubricate applicator well and gently insert applicator into rectum. Thoroughly cleanse applicator after each use.

Inactive Ingredients

Aloe Vera, Iodine, Okra, Oleic Acid, Sage

For Questions or Comments:

PDmerc.com

Distributed by

P D Merc, LLC

1581 W 49th St #191

Hialeah, FL 33012

NDC 50211-001-01

PACKAGE LABEL

Hemo-Fin

Hemorrhoidal Oitment

Net Wt. 1 oz. (28 g)

HemoFin20120910.jpg

HemoFin20120910.jpg